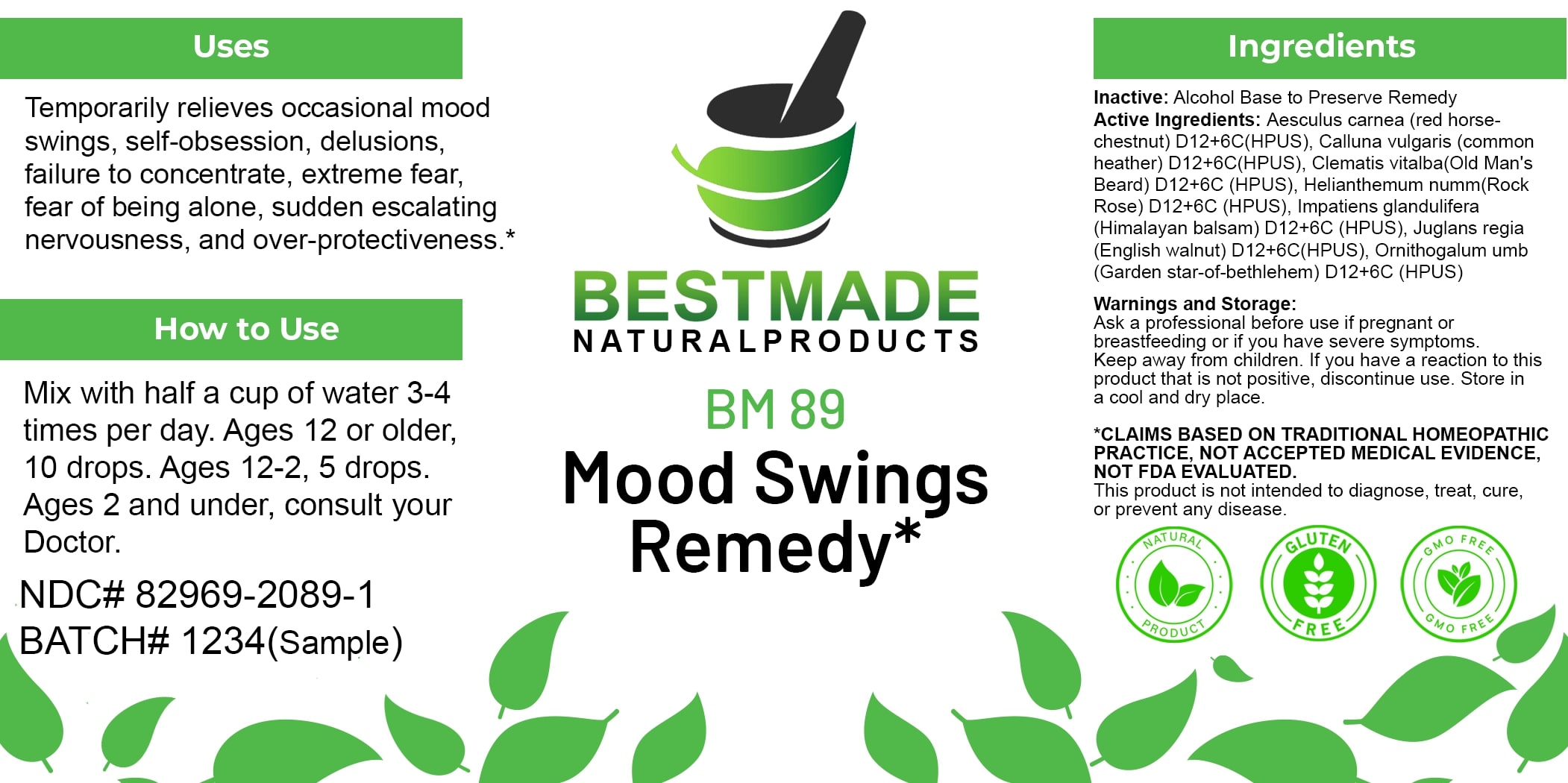 DRUG LABEL: Bestmade Natural Products BM89
NDC: 82969-2089 | Form: LIQUID
Manufacturer: Bestmade Natural Products
Category: homeopathic | Type: HUMAN OTC DRUG LABEL
Date: 20250203

ACTIVE INGREDIENTS: HELIANTHEMUM NUMMULARIUM WHOLE 6 [hp_C]/6 [hp_C]; CALLUNA VULGARIS FLOWERING TOP 6 [hp_C]/6 [hp_C]; ORNITHOGALUM UMBELLATUM 6 [hp_C]/6 [hp_C]; IMPATIENS GLANDULIFERA FLOWER 6 [hp_C]/6 [hp_C]; JUGLANS REGIA LEAF 6 [hp_C]/6 [hp_C]; AESCULUS CARNEA FLOWER 6 [hp_C]/6 [hp_C]; CLEMATIS VITALBA TOP 6 [hp_C]/6 [hp_C]
INACTIVE INGREDIENTS: ALCOHOL 6 [hp_C]/6 [hp_C]

BM89

DOSAGE AND ADMINISTRATION

How to Use

Mix with half a cup of water 3-4 times per day. Ages 12 or older, 10 drops. Ages 12-2, 5 drops. Ages 2 and under, consult your Doctor.

INACTIVE INGREDIENT

Ingredients

Inactive: Alcohol Base to Preserve Remedy

ACTIVE INGREDIENT

Active Ingredients: Aesculus carnea (red horse-chestnut) D12+6C (HPUS), Calluna vulgaris (common heather) D12+6C (HPUS), Clematis vitalba(Old Man's Beard) D12+6C (HPUS), Helianhemum numm(Rock Rose) D12+6C (HPUS), Impatiens glandulifera (Himalayan balsam) D12+6C (HPUS), Juglans regia (English walnut) D12+6C (HPUS), Ornithogalum umb (Garden star-of-bethlehem) D12+6C (HPUS)

Uses

Temporarily relieves occasional mood swings, self-obsession, delusions, failure to concentrate, extreme fear, fear of being alone, sudden escalating nervousness, and over-protectiveness.*

*CLAIMS BASED ON TRADITIONAL HOMEOPATHIC PRACTICE, NOT ACCEPTED MEDICAL EVIDENCE, NOT FDA EVALUATED.

This product is not intended to diagnose, treat, cure, or prevent any disease.

Uses

Temporarily relieves occasional mood swings, self-obsession, delusions, failure to concentrate, extreme fear, fear of being alone, sudden escalating nervousness, and over-protectiveness.*

*CLAIMS BASED ON TRADITIONAL HOMEOPATHIC PRACTICE, NOT ACCEPTED MEDICAL EVIDENCE, NOT FDA EVALUATED.

This product is not intended to diagnose, treat, cure, or prevent any disease.

KEEP OUT OF REACH OF CHILDREN

Warnings and Storage:

Ask a professional before use if pregnant or breastfeeding or if you have severe symptoms. Keep away from children. If you have a reaction to this product that is not positive, discontinue use. Store in a cool and dry place.

Warnings and Storage:

Ask a professional before use if pregnant or breastfeeding or if you have severe symptoms. Keep away from children. If you have a reaction to this product that is not positive, discontinue use. Store in a cool and dry place.

*CLAIMS BASED ON TRADITIONAL HOMEOPATHIC PRACTICE, NOT ACCEPTED MEDICAL EVIDENCE, NOT FDA EVALUATED.

This product is not intended to diagnose, treat, cure, or prevent any disease.

Entire package label